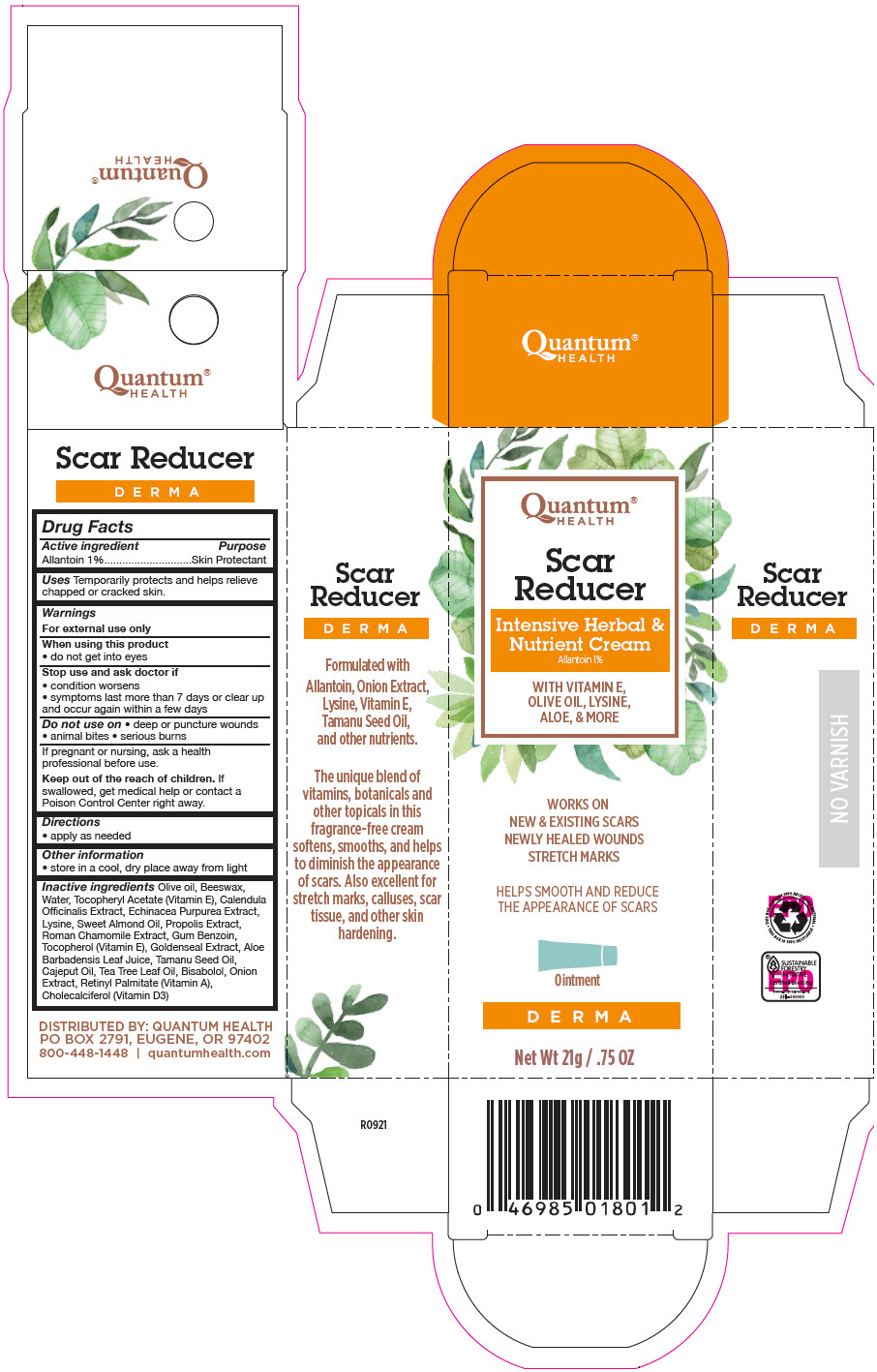 DRUG LABEL: Scar Reducer
NDC: 70084-710 | Form: CREAM
Manufacturer: Quantum, Inc
Category: otc | Type: HUMAN OTC DRUG LABEL
Date: 20251006

ACTIVE INGREDIENTS: ALLANTOIN 1 g/100 g
INACTIVE INGREDIENTS: OLIVE OIL; YELLOW WAX; WATER; .ALPHA.-TOCOPHEROL ACETATE; CALENDULA OFFICINALIS FLOWER; ECHINACEA ANGUSTIFOLIA WHOLE; LYSINE; ALMOND OIL; PROPOLIS WAX; CHAMAEMELUM NOBILE WHOLE; BENZOIN RESIN; TOCOPHEROL; GOLDENSEAL; ALOE VERA LEAF; TAMANU OIL; CAJUPUT OIL; TEA TREE OIL; LEVOMENOL; ONION; VITAMIN A PALMITATE; CHOLECALCIFEROL

Scar Reducer
Intensive Herbal & Nutrient

Drug Facts

Active ingredient

Allantoin 1%

Purpose

Skin Protectant

Uses

Temporarily protects and helps relieve chapped or cracked skin.

Warnings

For external use only

When using this product

- do not get into eyes

Stop use and ask doctor if

- condition worsens
- symptoms last more than 7 days or clear up and occur again within a few days

Do not use on

- deep or puncture wounds
- animal bites
- serious burns

PREGNANCY OR BREAST FEEDING

If pregnant or nursing, ask a health professional before use.

KEEP OUT OF REACH OF CHILDREN

Keep out of the reach of children.If swallowed, get medical help or contact a Poison Control Center right away.

Directions

- apply as needed

Other information

- store in a cool, dry place away from light

Inactive ingredients

Olive oil, Beeswax, Water, Tocopheryl Acetate (Vitamin E), Calendula Officinalis Extract, Echinacea Purpurea Extract, Lysine, Sweet Almond Oil, Propolis Extract, Roman Chamomile Extract, Gum Benzoin, Tocopherol (Vitamin E), Goldenseal Extract, Aloe Barbadensis Leaf Juice, Tamanu Seed Oil, Cajeput Oil, Tea Tree Leaf Oil, Bisabolol, Onion Extract, Retinyl Palmitate (Vitamin A), Cholecalciferol (Vitamin D3)

DISTRIBUTED BY: QUANTUM HEALTH
PO BOX 2791, EUGENE, OR 97402

PRINCIPAL DISPLAY PANEL - 21 g Tube Box

Quantum®
HEALTH

Scar
Reducer

Intensive Herbal &
Nutrient Cream
Allantoin 1%

WITH VITAMIN E,
OLIVE OIL, LYSINE,
ALOE, & MORE

WORKS ON
NEW & EXISTING SCARS
NEWLY HEALED WOUNDS
STRETCH MARKS

HELPS SMOOTH AND REDUCE
THE APPEARANCE OF SCARS

Ointment

D E R M A

Net Wt 21g / .75 OZ